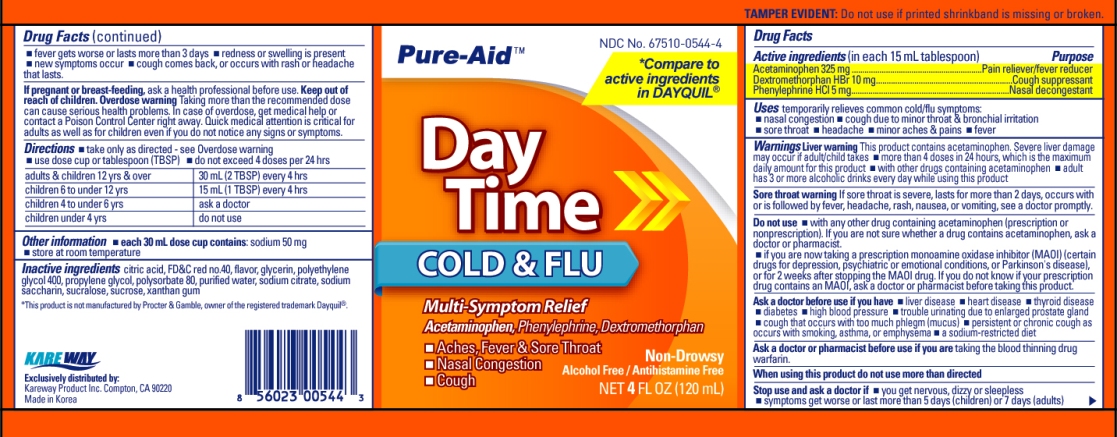 DRUG LABEL: Day Time Cold/Flu Relief
NDC: 67510-0544 | Form: LIQUID
Manufacturer: Kareway Product, Inc.
Category: otc | Type: HUMAN OTC DRUG LABEL
Date: 20120711

ACTIVE INGREDIENTS: ACETAMINOPHEN 325 mg/15 mL; DEXTROMETHORPHAN HYDROBROMIDE 10 mg/15 mL; PHENYLEPHRINE HYDROCHLORIDE 5 mg/15 mL
INACTIVE INGREDIENTS: CITRIC ACID MONOHYDRATE; FD&C RED NO. 40; GLYCERIN; POLYETHYLENE GLYCOLS; PROPYLENE GLYCOL; WATER; SODIUM CITRATE; SUCROSE; SUCRALOSE; SACCHARIN SODIUM DIHYDRATE; XANTHAN GUM

Drug Facts

Active ingredients(in each 15 ml tablespoon)

Acetaminophen 325mg

Dextromethorphan HBr 10mg

Phenylephrine HCl 5mg

Purpose

Pain reliever/fever reducer

Cough suppressant

Nasal decongestant

Uses

temporarily relieves common cold/flu symptoms:

- nasal decongestion
- cough due to minor throat and bronchial irritation
- sore throat
- headache
- minor aches and pains
- fever

Warnings

Enter section text here

Liver warning

This product contains acetaminophen. Severe liver damage may occur if adult/child takes

- more than 4 doses in 24 hrs, which is the maximum daily amount for this product
- with other drugs containing acetaminophen
- adult has 3 or more alcoholic drinks every day while using this product

Sore throat warning:

If sore throat is severe, lasts for more than 2 days, occurs with or is followed by fever, headache, rash, nausea, or vomiting, see a doctor promptly.

Do not use

- with any other drug containing acetaminophen(prescription or nonprescription). If you are not sure whether a drug contains acetaminophen, ask a doctor or pharmacist.
- if you are now taking a prescription monoamine oxidase inhibitor (MAOI)(certain drugs for depression, psychiatric or emotional conditions, or Parkinson's disease), or for 2 weeks after stopping the MAOI drug. If you do not know if your prescription drug contains an MAOI, ask a doctor or pharmacist before taking this product.

Ask a doctor before use if you have

- liver disease
- heart disease
- thyroid disease
- diabetes
- high blood pressure
- trouble urinating due to enlarged prostate gland
- cough that occurs with too much phegm(mucus)
- Persistent or chronic cough as occurs with smoking, asthma, emphysema
- a sodium-restricted diet

Ask a doctor or pharmacist before use if you are

taking the blood thinning drug warfarin.

Stop use and ask a doctor if

- you get nervous, dizzy or sleepless
- symptoms get worse or last more than 5 days (children) or 7 days (adults)
- fever gets worse or lasts more than 3 days
- redness or swelling is present
- new symptoms occur
- cough comes back or occurs with rash or headache that lasts. These could be signs of a serious condition.

If pregnant or breast-feeding,

ask a health professional before use.

Keep out of reach of children.

Enter section text here

Overdose warning:

Taking more than directed can cause serious health problems. In case of overdose, get medical help or contact a Poison Control Center right away. Quick medical attention is critical for adults and children even if you do not notice any signs or symptoms.

Directions

- take only as directed-see Overdose warning
- use dose cup or tablespoon (TBSP)
- do not exceed 4 doses per 24 hours
  adults and children 12 yrs and over | 30 ml (2 TBSP) every 6 hours
  children 6 to under 12 yrs | 15 ml (1 TBSP) every 4 hours
  children 4 to under 6 yrs | ask a doctor
  children under 4 yrs | do not use

Other information

- each tablespoon contains: sodium 50mg
- store at room temperature

Inactive ingredients

citric acid, FDC red no.40, flavor, glycerin, polyethylene glycol, propylene glycol, purified water, saccharin sodium,
sodium citrate, sucralose, sucrose, xanthan gum

PACKAGE LABEL

Daytime Cold/Flu Relief